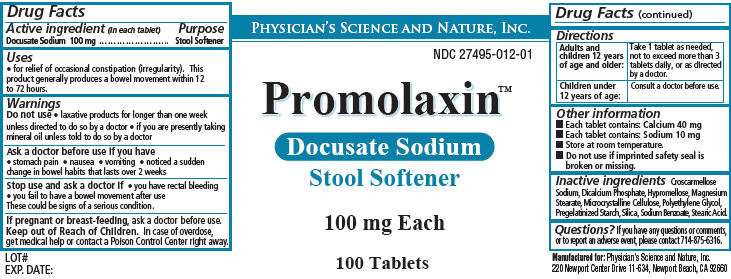 DRUG LABEL: Promolaxin
NDC: 27495-012 | Form: TABLET
Manufacturer: Physicians Science & Nature Inc.
Category: otc | Type: HUMAN OTC DRUG LABEL
Date: 20251111

ACTIVE INGREDIENTS: DOCUSATE SODIUM 100 mg/1 1
INACTIVE INGREDIENTS: HYPROMELLOSES; CROSCARMELLOSE SODIUM; ANHYDROUS DIBASIC CALCIUM PHOSPHATE; MAGNESIUM STEARATE; CELLULOSE, MICROCRYSTALLINE; POLYETHYLENE GLYCOL; STARCH, CORN; SILICON DIOXIDE; SODIUM BENZOATE; STEARIC ACID

Promolaxin™ Docusate Sodium Stool Softener

Active ingredient

Docusate Sodium 100 mg

Purpose

Stool Softener

Uses

- for relief of occasional constipation (irregularity). This product generally produces a bowel movement within 12 to 72 hours.

Do not use

- laxative products for longer than one week unless directed to do so by a doctor
- if you are presently taking mineral oil unless told to do so by a doctor

Ask a doctor before use if you have

- stomach pain
- nausea
- vomiting
- noticed a sudden change in bowel habits that lasts over 2 weeks

Stop use and ask a doctor if

- you have rectal bleeding
- you fail to have a bowel movement after use
  These could be signs of a serious condition.

If pregnant or breast-feeding,

ask a doctor before use.

Keep out of Reach of Children.

In case of overdose, get medical help or contact a Poison Control Center right away.

Directions

Adults andchildren 12 yearsof age and older:

Take 1 tablet as needed, not to exceed more than 3 tablets daily, or as directed by a doctor.

Children under 12 years of age:

Consult a doctor before use.

Other information

- Each tablet contains: Calcium 40 mg
- Each tablet contains: Sodium 10 mg
- Store at room temperature.
- Do not use if imprinted safety seal is broken or missing.

Inactive ingredients

Croscarmellose Sodium, Dicalcium Phosphate, Hypromellose, Magnesium Stearate, Microcrystalline Cellulose, Polyethylene Glycol, Pregelatinized Starch, Silica, Sodium Benzoate, Stearic Acid.

Questions?

If you have any questions or comments, or to report an adverse event,

please contact 714-875-6316.

Manufactured for:Physician's Science and Nature, Inc.

220 Newport Center Drive 11-634, Newport Beach, CA 92660

Package/Label Principal Display Panel

Physician's Science and Nature, Inc.

NDC 27495-012-01

Promolaxin™

Docusate Sodium

Stool Softener

100 mg Each

100 Tablets